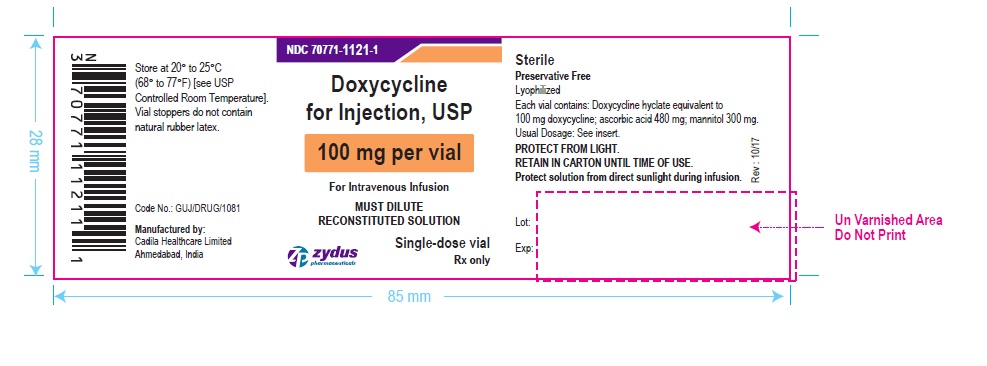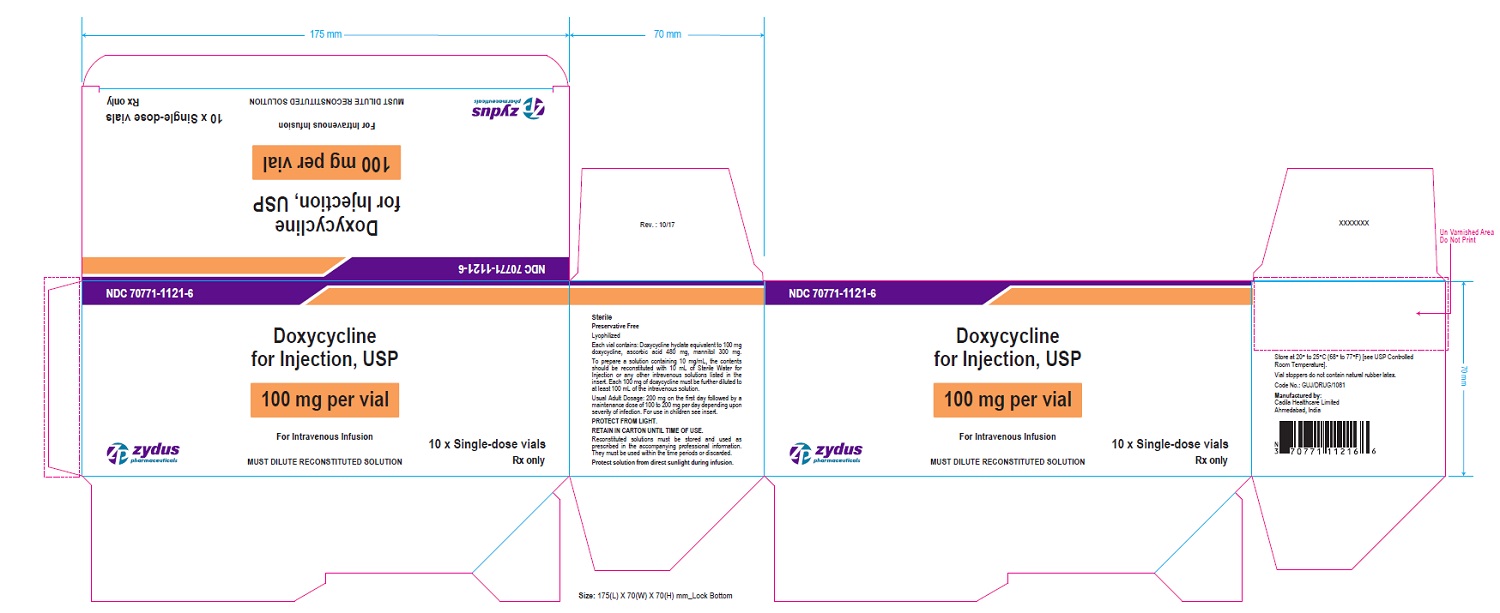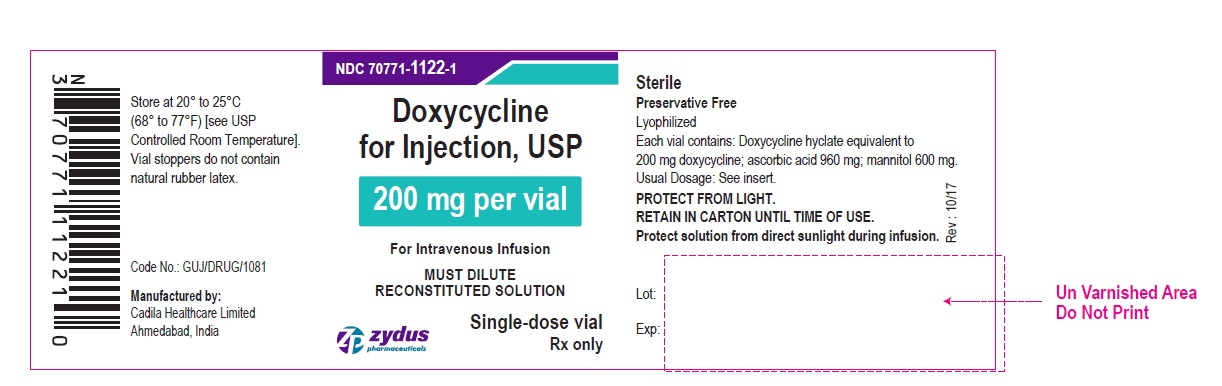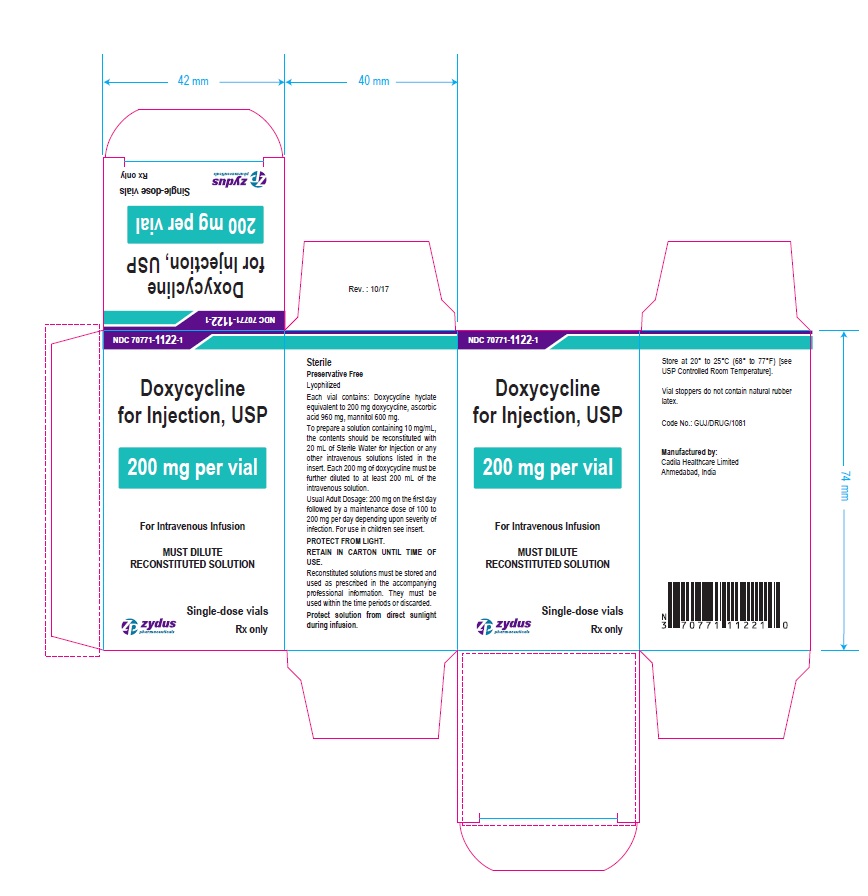 DRUG LABEL: Doxycycline
NDC: 70771-1121 | Form: INJECTION, POWDER, LYOPHILIZED, FOR SOLUTION
Manufacturer: Zydus Lifesciences Limited
Category: prescription | Type: HUMAN PRESCRIPTION DRUG LABEL
Date: 20221105

ACTIVE INGREDIENTS: DOXYCYCLINE HYCLATE 100 mg/10 mL
INACTIVE INGREDIENTS: ASCORBIC ACID 480 mg/10 mL; MANNITOL 300 mg/10 mL

Doxycycline For Injection USP

PACKAGE LABEL-PRINCIPAL DISPLAY PANEL – DOXYCYCLINE 100 MG CONTAINER LABEL

NDC 70771-1121-1

Doxycycline for Injection, USP

100 mg per vial

For Intravenous Infusion

MUST DILUTE RECONSTITUTED SOLUTION

Single-dose vial

Rx only

Zydus Pharmaceuticals

PACKAGE LABEL-PRINCIPAL DISPLAY PANEL - DOXYCYCLINE 100 MG CARTON LABEL

NDC 70771-1121-6

Doxycycline for Injection, USP

100 mg per vial

For Intravenous Infusion

MUST DILUTE RECONSTITUTED SOLUTION

10 x Single-dose vials

Rx only

Zydus Pharmaceuticals

PACKAGE LABEL-PRINCIPAL DISPLAY PANEL – DOXYCYCLINE 200 MG CONTAINER LABEL

NDC 70771-1122-1

Doxycycline for Injection, USP

200 mg per vial

For Intravenous Infusion

MUST DILUTE RECONSTITUTED SOLUTION

Single-dose vial

Rx only

Zydus Pharmaceuticals

PACKAGE LABEL-PRINCIPAL DISPLAY PANEL - DOXYCYCLINE 200 MG CARTON LABEL

NDC 70771-1122-1

Doxycycline for Injection, USP

200 mg per vial

For Intravenous Infusion

MUST DILUTE RECONSTITUTED SOLUTION

Single-dose vial

Rx only

Zydus Pharmaceuticals